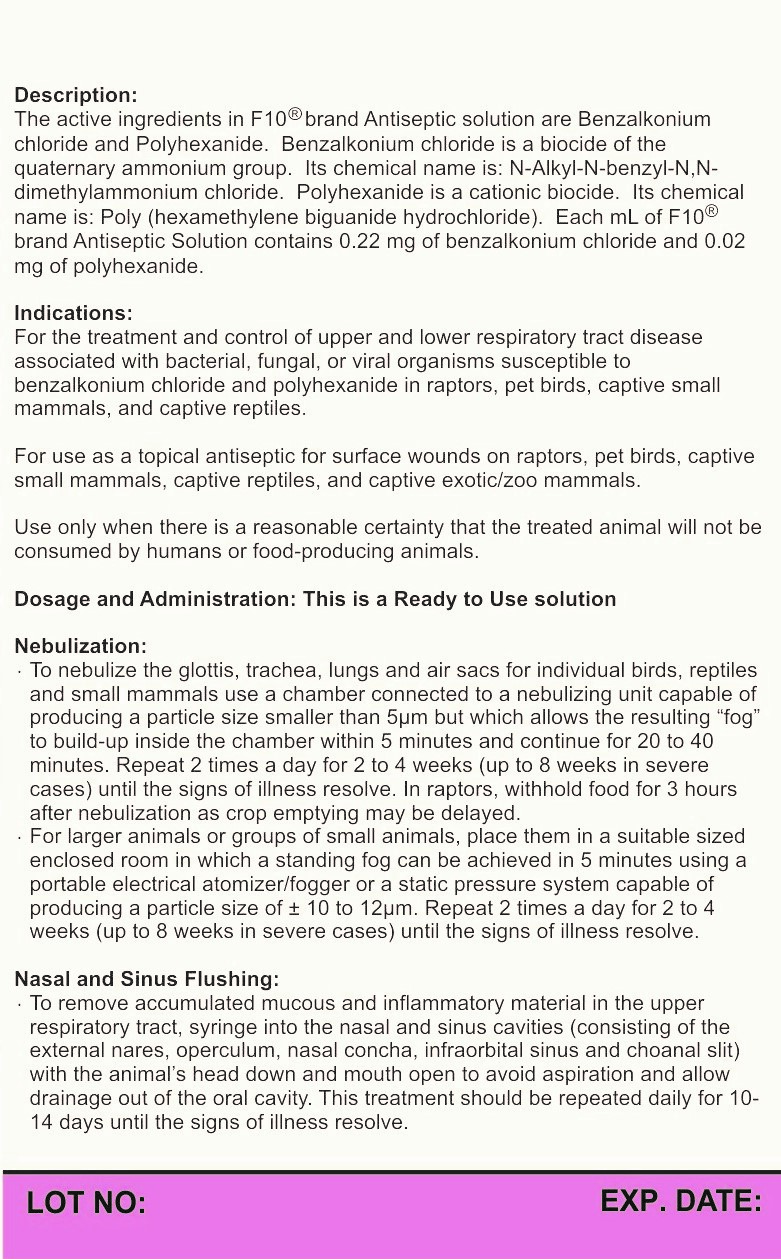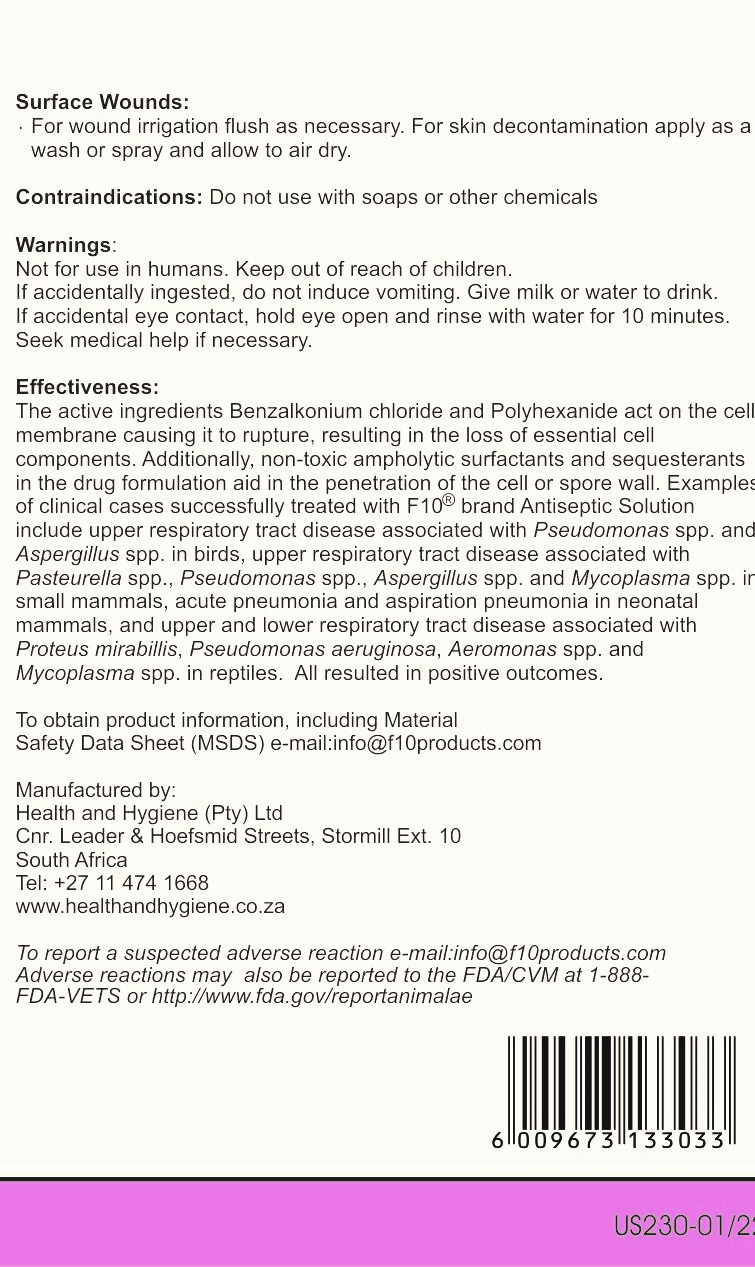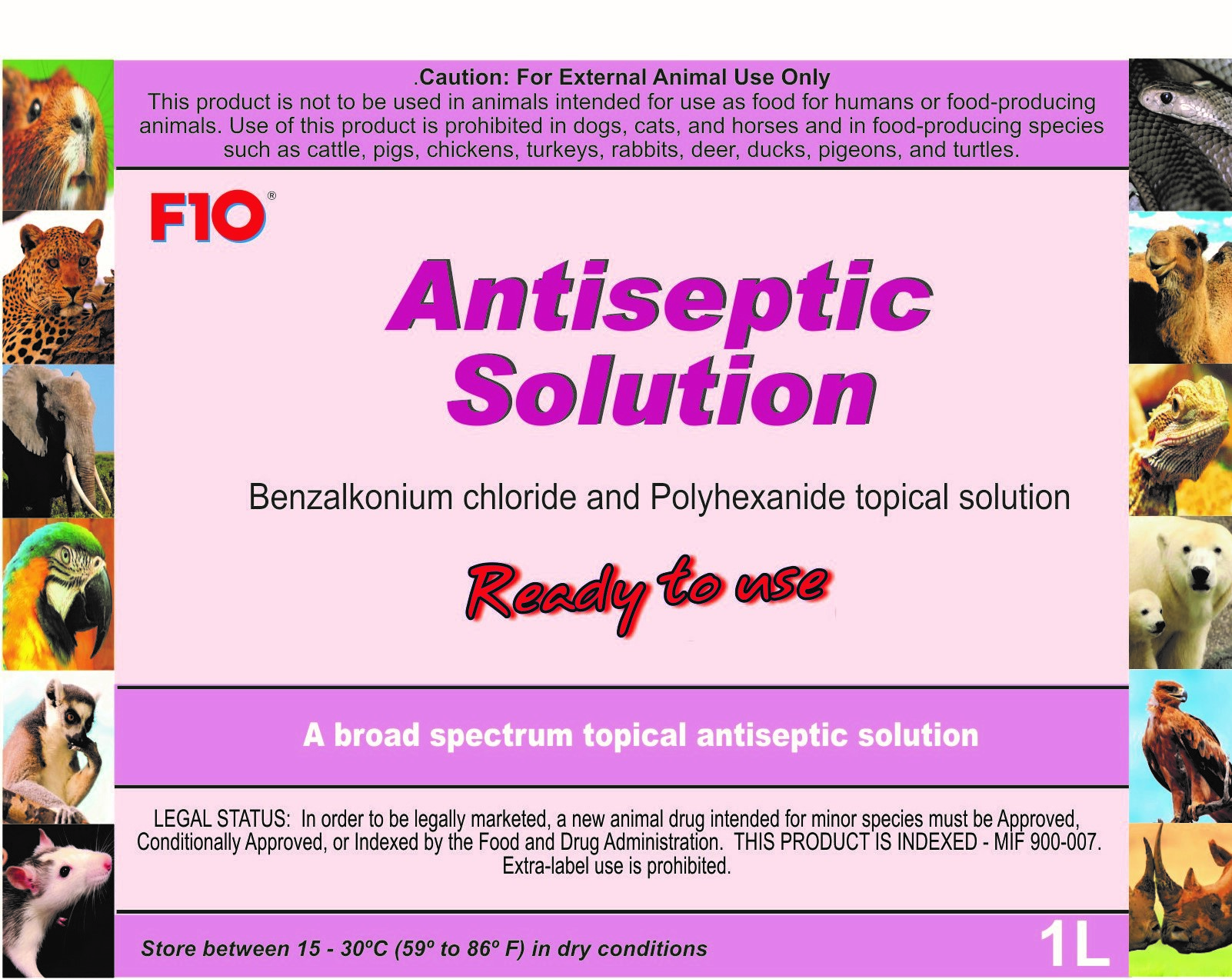 DRUG LABEL: F10
NDC: 86152-0072 | Form: LIQUID
Manufacturer: Health and Hygiene (Pty) Ltd
Category: animal | Type: PRESCRIPTION ANIMAL DRUG LABEL
Date: 20220128

ACTIVE INGREDIENTS: BENZALKONIUM CHLORIDE 0.22 g/1 L; BIGUANIDE 0.02 g/1 L

F10 Antiseptic Solution Ready to use

Warning

Not for use in humans. Keep out of reach of children

Uses

For the treatment and control of upper and lower respiratory tract diseases associated with bacterial, fungal, or viral organisms.
For use as a topical antiseptic for surface wounds.

Directions of Use

Use for Nebulization, nasal and sinus flushing and surface wounds.
See label for further instructions

Packaging Label

Front Panel

US230-01 22 ANTISEPTIC SOLUTION RTU-1L GENERIC FP.jpg

Packaging Label

Back Panel 1

US230-01 22 ANTISEPTIC SOLUTION RTU-1L GENERIC BP1.jpg

Packaging Label

Back Panel 2

US230-01 22 ANTISEPTIC SOLUTION RTU-1L GENERIC BP2.jpg